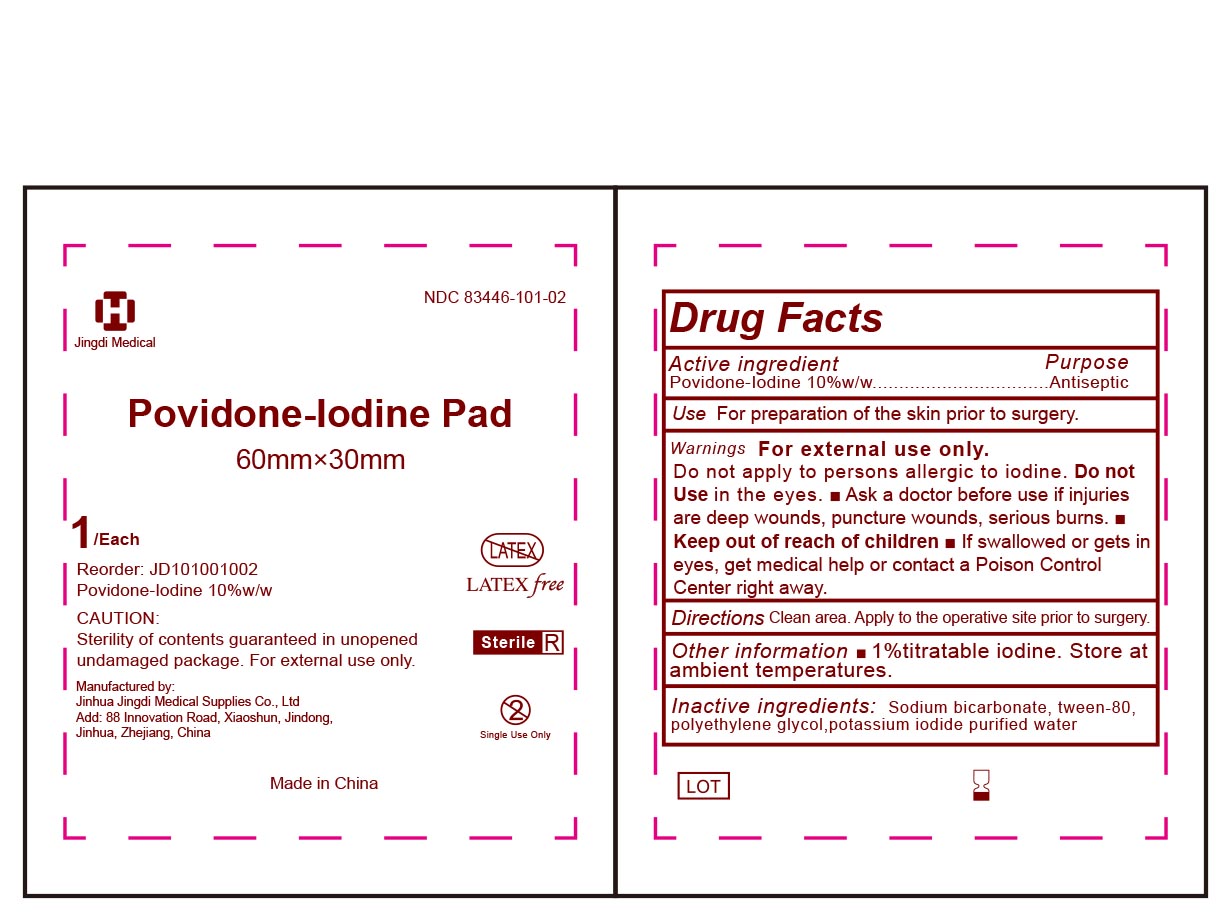 DRUG LABEL: Povidone-Iodine Pad Sterile
NDC: 83446-101 | Form: CLOTH
Manufacturer: JINHUA JINGDI MEDICAL SUPPLIES CO., LTD
Category: otc | Type: HUMAN OTC DRUG LABEL
Date: 20260101

ACTIVE INGREDIENTS: POVIDONE-IODINE 10 g/100 g
INACTIVE INGREDIENTS: SODIUM BICARBONATE; POLYSORBATE 80; POTASSIUM IODIDE; POLYETHYLENE GLYCOL 400; WATER

ACTIVE INGREDIENT

Povidone-lodine 10%w/w

DESCRIPTION

Use for preparation of the skin prior to surgery.

Sterile in unopened, undamaged package.
Not made with natural rubber latex.

INACTIVE INGREDIENT

Sodium bicarbonate, polysorbate-80, polyethylene glycol, potassium iodide, purified water

PURPOSE

Antiseptic

For preparation of the skin prior to surgery

WARNINGS

For external use only.

Do not apply to persons allergic to iodine.

Keep out of reach of children

If swallowed or gets in eyes, get medical help or contact a Poison Control Center right away.

Directions

Clean area. Apply to the operative site prior to surgery.

Do not Use in the eyes.

Ask a doctor before use if injuries are deep wounds, puncture wounds, serious burns.

OTHER SAFETY INFORMATION

1% titratable iodine.

Store at ambient temperature.

DOSAGE AND ADMINISTRATION

Apply topically as needed to cleanse intendend area；
Apply the product to the skin, take the injection or puncture site as the center, slowly rotate from the insideto the outside, and gradually apply the product for two times, the disinfection area should be more than5cmx5cm, and the action time should be 1min.